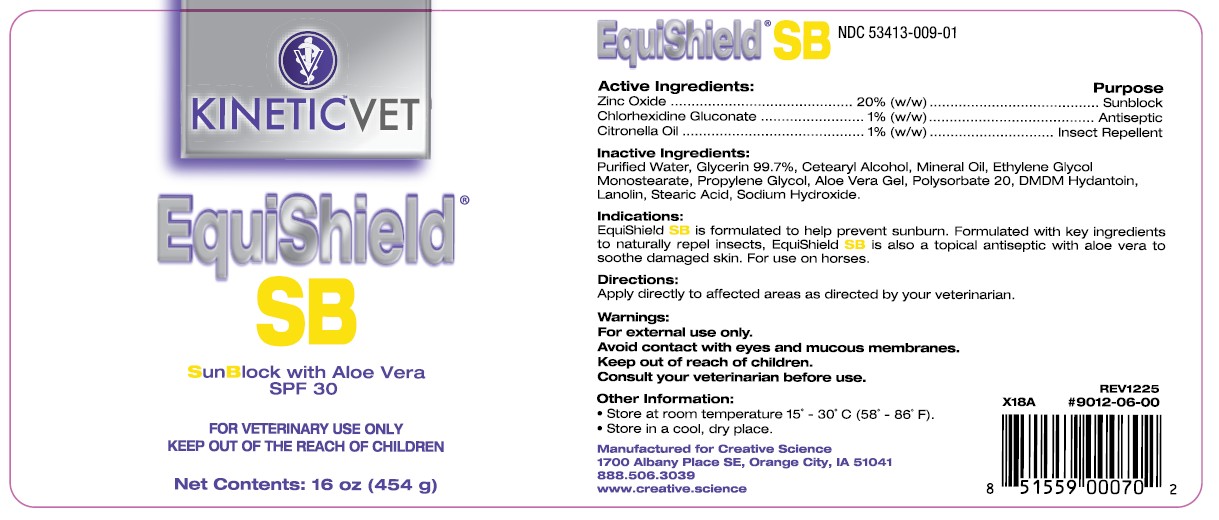 DRUG LABEL: EquiShield SB
NDC: 53413-009 | Form: CREAM
Manufacturer: Creative Science
Category: animal | Type: OTC ANIMAL DRUG LABEL
Date: 20251223

ACTIVE INGREDIENTS: ZINC OXIDE 20 g/100 g; CHLORHEXIDINE GLUCONATE 1 g/100 g; CITRONELLA OIL 1 g/100 g

EquiShield SB

NDC 53413-009-01

Active Ingredients:

Zinc Oxide.................................... 20% (w/w)

Chlorhexidine Gluconate................... 1% (w/w)

Citronella Oil................................... 1% (w/w)

Purpose

..................Sunblock

.................Antiseptic

.........Insect Repellent

Inactive Ingredients:

Purified Water, Glycerin 99.7%, Cetearyl Alcohol, Mineral Oil, Ethylene Glycol Monostearate, Propylene Glycol, Aloe Vera Gel, Polysorbate 20, DMDM Hydantoin, Lanolin, Stearic Acid, Sodium Hydroxide.

Indications:

EquiShield SB is formulated to help prevent sunburn. Formulated with key ingredients to naturally repel insects, EquiShield SB is also a topical antiseptic with aloe vera to soothe damaged skin. For use on horses.

Directions:

Apply directly to affected areas as directed by your veterinarian.

Warnings:

For external use only.

Avoid contact with eyes and mucous membranes.

Keep out of reach of children.

Consult your veterinarian before use.

Other Information:

• Store at room temperature 15° - 30°C (58° - 86°F)

• Store in a cool, dry place

REV 1225 #9012-06-00 UPC 851559000702

Manufactured for Creative Science

1700 Albany Place SE, Orange City, IA 51041

888.506.3039

www.creative.science

PACKAGE LABEL

EquiShield® SB

SunBlock with Aloe Vera

SPF 30

FOR VETERINARY USE ONLY

KEEP OUT OF THE REACH OF CHILDREN

Net Contents: 16 oz (454 g)